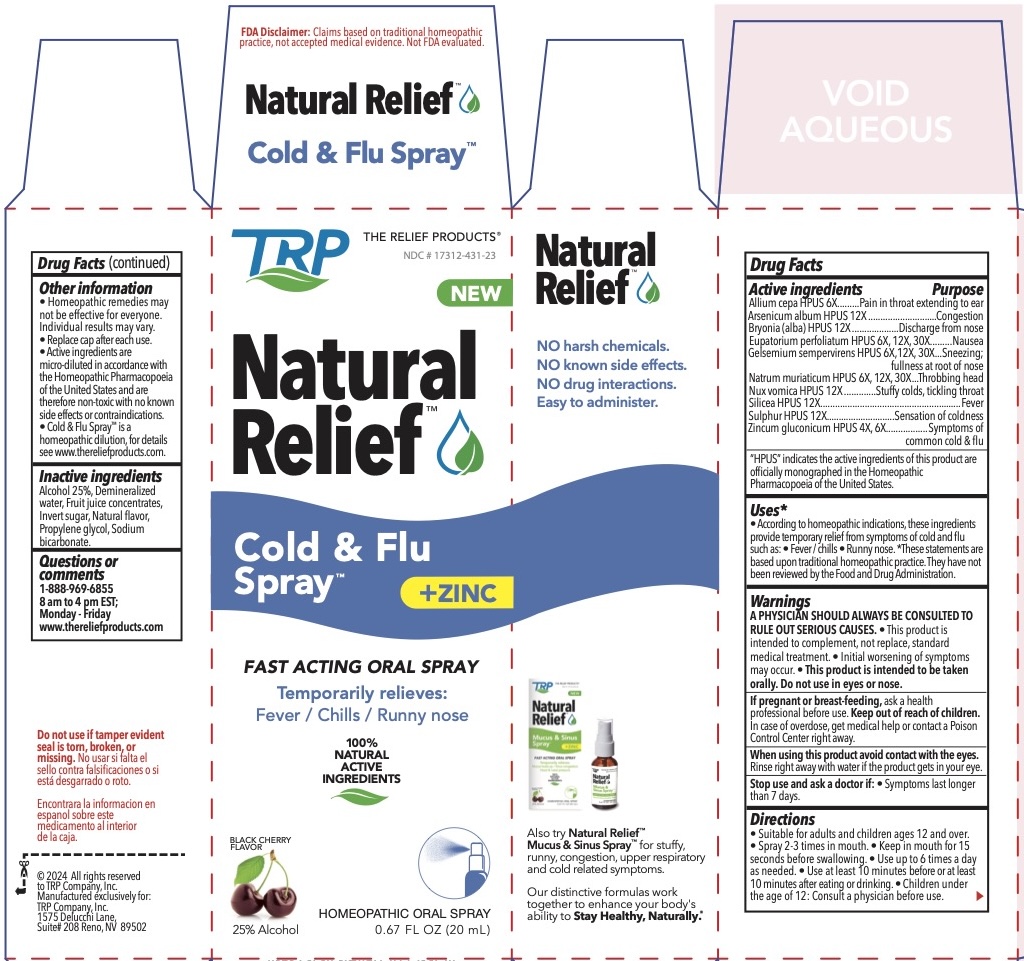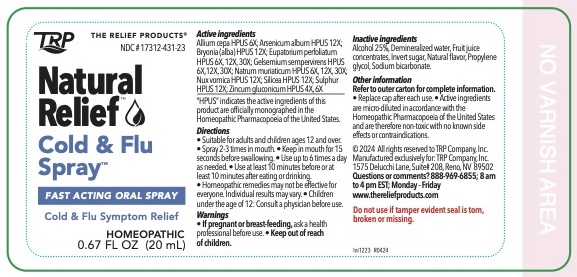 DRUG LABEL: Natural Relief Cold and Flu
NDC: 17312-431 | Form: SPRAY
Manufacturer: TRP Company
Category: homeopathic | Type: HUMAN OTC DRUG LABEL
Date: 20251215

ACTIVE INGREDIENTS: ALLIUM CEPA WHOLE 6 [hp_X]/1 mL; SILICON DIOXIDE 12 [hp_X]/1 mL; STRYCHNOS NUX-VOMICA SEED 12 [hp_X]/1 mL; SODIUM CHLORIDE 6 [hp_X]/1 mL; BRYONIA ALBA ROOT 12 [hp_X]/1 mL; GELSEMIUM SEMPERVIRENS WHOLE 6 [hp_X]/1 mL; EUPATORIUM PERFOLIATUM FLOWERING TOP 6 [hp_X]/1 mL; ARSENIC TRIOXIDE 12 [hp_X]/1 mL; SULFUR 12 [hp_X]/1 mL; ZINC GLUCONATE 4 [hp_X]/1 mL
INACTIVE INGREDIENTS: INVERT SUGAR; WATER; ALCOHOL; PROPYLENE GLYCOL; SODIUM BICARBONATE

TRP Natural Relief ® Cold & Flu Spray™

ACTIVE INGREDIENTS:

Allium cepa HPUS 6X, Arsenicum album HPUS 12X, Bryonia alba HPUS 12X, Eupatorium perfoliatum HPUS 6X, 12X, 30X, Gelsemium sempervirens HPUS 6X, 12X, 30X, Natrum muriaticum HPUS 6X, 12X, 30X, Nux vomica HPUS 12X, Silicea HPUS 12X, Sulphur HPUS 12X, Zincum gluconicum HPUS 4X, 6X

USES:

• According to homeopathic indications, these ingredients provide temporary relief from symptoms of cold and flu such as: • Fever / chills • Runny nose.

*These statements are based upon traditional homeopathic practice. They have not been reviewed by the Food and Drug Administration.

WARNINGS:

A PHYSICIAN SHOULD ALWAYS BE CONSULTED TO RULE OUT SERIOUS CAUSES. • This product is intended to complement, not replace, standard medical treatment. • Initial worsening of symptoms may occur. • This product is intended to be taken orally. Do not use in eyes or nose.

When using

When using this product avoid contact with the eyes.

Rinse right away with water if the product gets in your eye.

Keep out of reach of children. In case of overdose, get medical help or call a Poison Control Center right away.

Pregnancy warning

If pregnant or breast-feeding, ask a health professional before use.

DIRECTIONS:

Suitable for adults and children ages 12 and over.
Spray 2-3 times in mouth. • Keep in mouth for 15 seconds before swallowing. • Use up to 6 times a day as needed. • Use at least 10 minutes before or at least 10 minutes after eating or drinking.

• Children under the age of 12: Consult a physician before use.

INDICATIONS:

Uses*

• According to homeopathic indications, these ingredients provide temporary relief from symptoms of cold and flu such as: • Fever / chills • Runny nose. *These statements are based upon traditional homeopathic practice. They have not been reviewed by the Food and Drug Administration.

Stop use

Stop use and ask a doctor if: • Symptoms last longer than 7 days.

INACTIVE INGREDIENTS:

Alcohol 25%, Demineralized water, Fruit juice concentrates, Invert sugar, Natural flavor, Propylene glycol, Sodium bicarbonate.

Other information

• Homeopathic remedies may not be effective for everyone. Individual results may vary.

• Replace cap after each use.
• Active ingredients are micro-diluted in accordance with the Homeopathic Pharmacopoeia of the United States and are therefore non-toxic with no known side effects or contraindications.
• Cold & Flu SprayTM is a homeopathic dilution, for details see www.thereliefproducts.com.

QUESTIONS:

Questions or comments

1-888-969-6855

8 am to 4 pm EST;

Monday - Friday

www.thereliefproducts.com